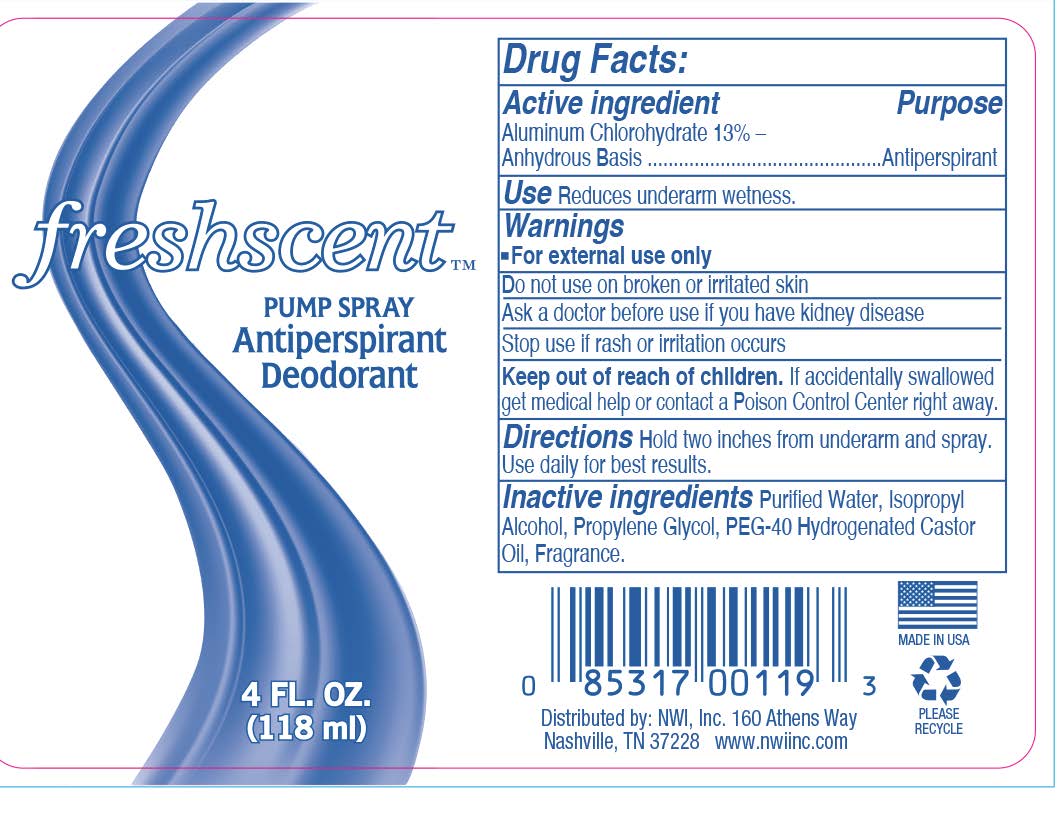 DRUG LABEL: Freshscent Anti-Perspirant Deodorant
NDC: 51824-023 | Form: SPRAY
Manufacturer: New World Imports, Inc.
Category: otc | Type: HUMAN OTC DRUG LABEL
Date: 20260112

ACTIVE INGREDIENTS: ALUMINUM CHLOROHYDRATE 13 g/100 mL
INACTIVE INGREDIENTS: WATER; ISOPROPYL ALCOHOL; PROPYLENE GLYCOL; PEG-40 CASTOR OIL

Freshscent Anti-Perspirant Deodorant

Drug Facts

Active ingredient

Aluminum Chlorohydrate 13% – Anhydrous Basis

Purpose

Antiperspirant

Use

Reduces underarm wetness.

Warnings

For external use only.

Keep out of reach of children. If accidentally swallowed get medical help or contact a Posion Control Center right away.

Do not use on broken skin or irritated skin

Stop use if rash or irritation occurs.

Ask a doctor before use if you have kidney disease.

Directions

Hold two inches from underarm and spray. Use daily for best results.

Inactive ingredients

Purified Water, Isopropyl Alcohol, Propylene Glycol, PEG-40 Hydrogenated Castor Oil, Fragrance.

Distributed by: NWI, Inc.
Nashville, TN 37228